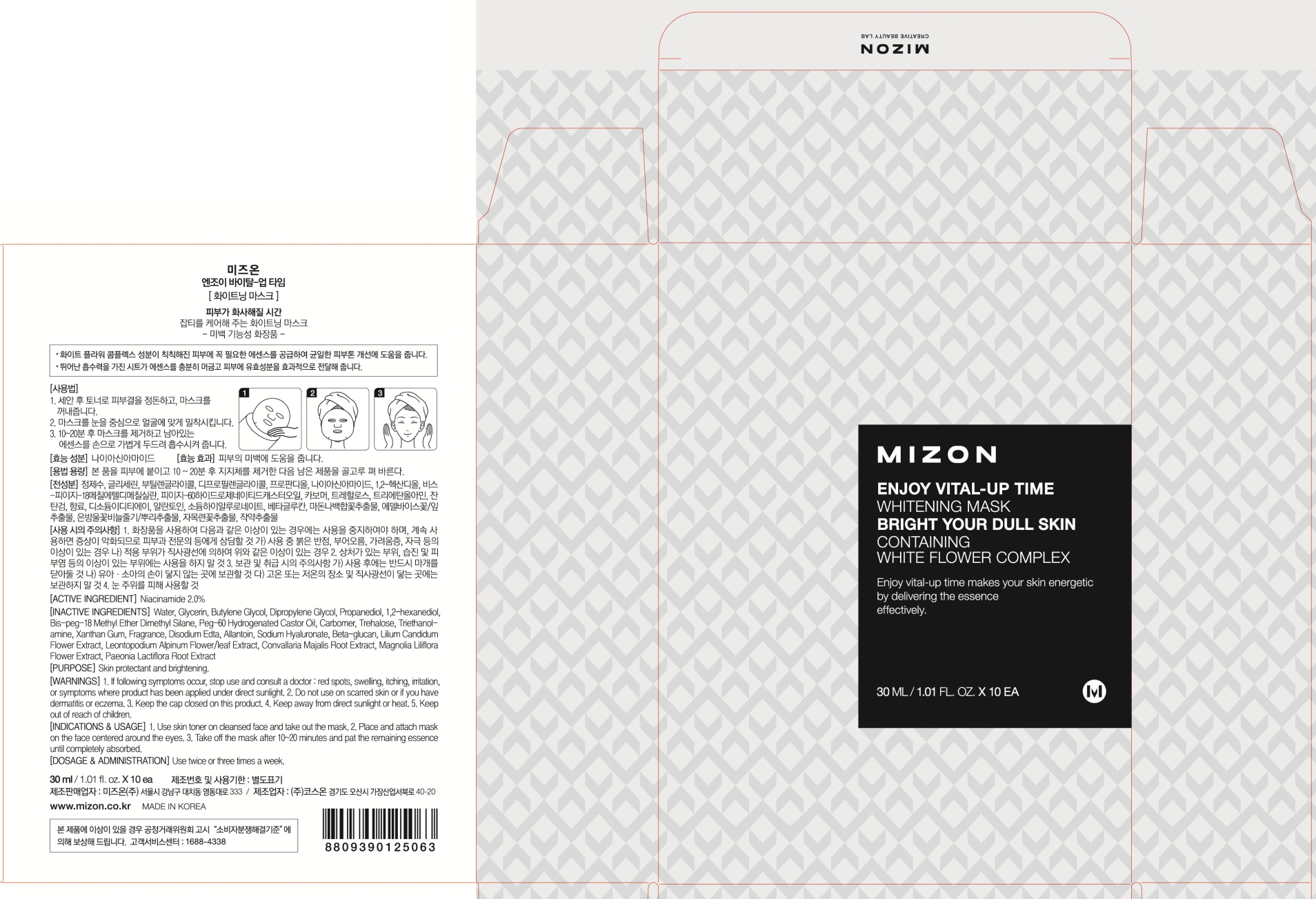 DRUG LABEL: MIZON ENJOY VITAL UP TIME Whitening Mask
NDC: 57718-110 | Form: PATCH
Manufacturer: MIZON CO., LTD.
Category: otc | Type: HUMAN OTC DRUG LABEL
Date: 20160323

ACTIVE INGREDIENTS: NIACINAMIDE 0.6 g/10 1
INACTIVE INGREDIENTS: WATER; GLYCERIN

ACTIVE INGREDIENT

Active Ingredient: NIACINAMIDE 2.0%

INACTIVE INGREDIENT

Inactive Ingredients: WATER, GLYCERIN, BUTYLENE GLYCOL, DIPROPYLENE GLYCOL, PROPANEDIOL, 1,2-HEXANEDIOL, BIS-PEG-18 METHYL ETHER DIMETHYL SILANE, PEG-60 HYDROGENATED CASTOR OIL, CARBOMER, TREHALOSE, TRIETHANOLAMINE, XANTHAN GUM, FRAGRANCE, DISODIUM EDTA, ALLANTOIN, SODIUM HYALURONATE, BETA-GLUCAN, LILIUM CANDIDUM FLOWER EXTRACT, LEONTOPODIUM ALPINUM FLOWER/LEAF EXTRACT, CONVALLARIA MAJALIS ROOT EXTRACT, MAGNOLIA LILIFLORA FLOWER EXTRACT, PAEONIA LACTIFLORA ROOT EXTRACT

PURPOSE

Purpose: Skin protectant and brightening

WARNINGS

Warnings: 1. If following symptoms occur, stop use and consult a doctor: red spots, swelling, itching, irritation, or symptoms where product has been applied under direct sunlight. 2. Do not use on scarred skin or if you have dermatitis or eczema. 3. Keep the cap closed on this product. 4. Keep away from direct sunlight or heat. 5. Keep out of reach of children.

KEEP OUT OF REACH OF CHILDREN

INDICATIONS & USAGE

Indications & Usage: 1. Use skin toner on cleansed face and take out the mask. 2. Place and attach mask on the face centered around the eyes. 3. Take off the mask after 10~20 minutes and pat the remaining essence until completely absorbed.

DOSAGE & ADMINISTRATION

Dosage & Administration: Use twice or three times a week.